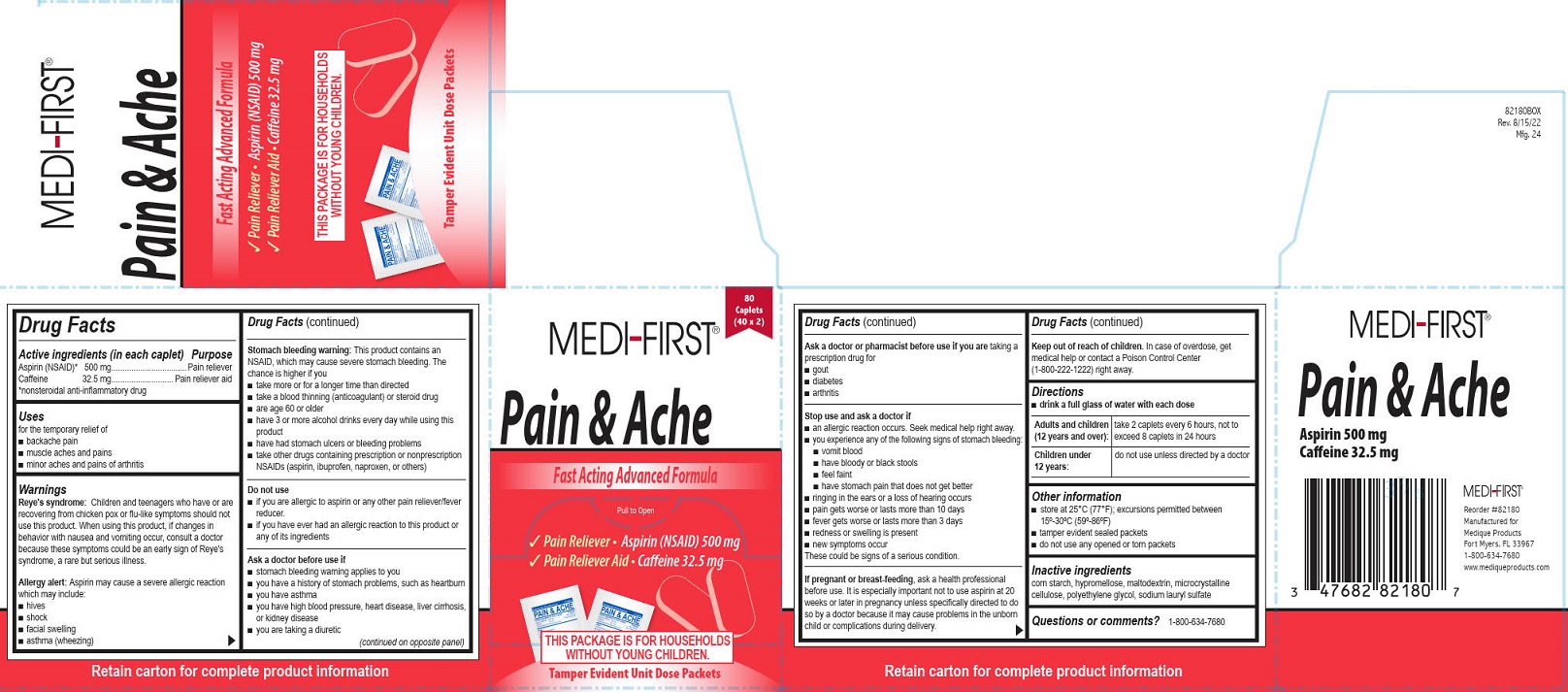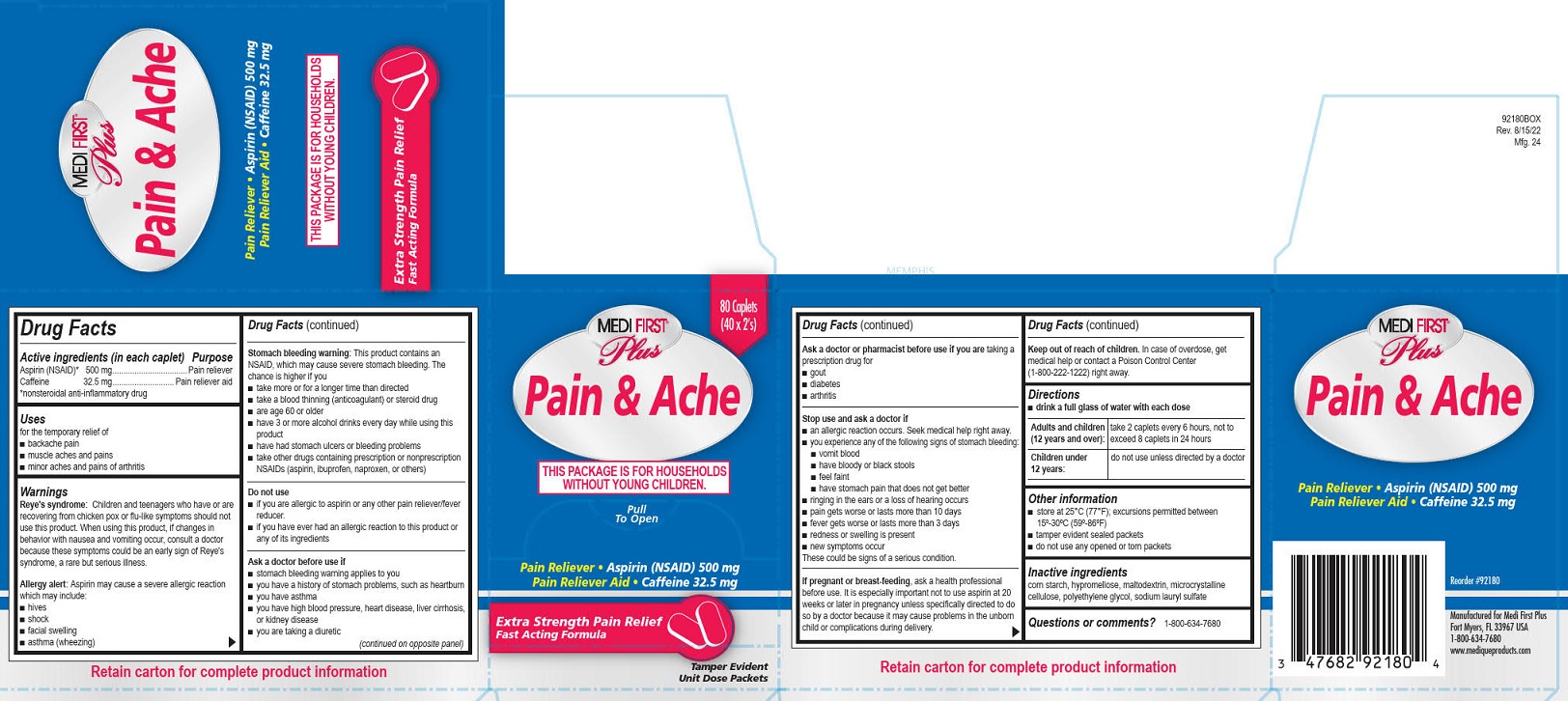 DRUG LABEL: Medi First Plus Pain Ache
NDC: 47682-921 | Form: TABLET, FILM COATED
Manufacturer: Unifirst First Aid Corporation
Category: otc | Type: HUMAN OTC DRUG LABEL
Date: 20250909

ACTIVE INGREDIENTS: ASPIRIN 500 mg/1 1; CAFFEINE 32.5 mg/1 1
INACTIVE INGREDIENTS: STARCH, CORN; HYPROMELLOSE, UNSPECIFIED; MALTODEXTRIN; POLYETHYLENE GLYCOL, UNSPECIFIED; MICROCRYSTALLINE CELLULOSE; SODIUM LAURYL SULFATE

Medi-First/Medi-First Plus Pain & Ache

Drug Facts

Active ingredients (in each caplet)

Aspirin (NSAID)* 500 mg

Caffeine 32.5 mg

*nonsteroidal anti-inflammatory drug

Purpose

Pain reliever

Pain reliever aid

Uses
for the temporary relief of
■ backache pain
■ muscle aches and pains
■ minor aches and pains of arthritis

Warnings

Reye's syndrome: Children and teenagers who have or are recovering from chicken pox or flu-like symptoms should not use this product. When using this product, if changes in behavior with nausea and vomiting occur, consult a doctor because these symptoms could be an early sign of Reye's syndrome, a rare but serious illness.

Allergy alert:

Aspirin may cause a severe allergic reaction which may include:

■ hives

■ shock

■ facial swelling

■ asthma (wheezing)

Stomach bleeding warning:

This product contains an NSAID, which may cause severe stomach bleeding. The chance is higher if you

■ take more or for a longer time than directed

■ take a blood thinning (anticoagulant) or steroid drug

■ are age 60 or older

■ have 3 or more alcohol drinks every day while using this product

■ have had stomach ulcers or bleeding problems

■ take other drugs containing prescription or nonprescription NSAIDs (aspirin, ibuprofen, naproxen, or others)

Do not use
■ if you are allergic to aspirin or any other pain reliever/fever reducer.
■ if you have ever had an allergic reaction to this product or any of its ingredients

Ask a doctor before use if

■ stomach bleeding warning applies to you

■ you have a history of stomach problems, such as heartburn

■ you have asthma

■ you have high blood pressure, heart disease, liver cirrhosis, or kidney disease

■ you are taking a diuretic

Ask a doctor or pharmacist before use if you are taking a prescription drug for
■ gout
■ diabetes
■ arthritis

Stop use and ask a doctor if

■ an allergic reaction occurs. Seek medical help right away.

■ you experience any of the following signs of stomach bleeding: ■ vomit blood ■ have bloody or black stools ■ feel faint ■ have stomach pain that does not get better

■ ringing in the ears or a loss of hearing occurs

■ pain gets worse or lasts more than 10 days

■ fever gets worse or lasts more than 3 days

■ redness or swelling is present

■ new symptoms occur

These could be signs of a serious condition.

PREGNANCY OR BREAST FEEDING

If pregnant or breast-feeding, ask a health professional before use. It is especially important not to use aspirin at 20 weeks or later in pregnancy unless specifically directed to do so by a doctor because it may cause problems in the unborn child or complications during delivery.

Keep out of reach of children. In case of overdose, get medical help or contact a Poison Control Center
(1-800-222-1222) right away.

Directions

■ drink a full glass of water with each dose

Adults and children (12 years and over): take 2 caplets every 6 hours, not to exceed 8 caplets in 24 hours

Children under 12 years: do not use unless directed by a doctor

Other information

■ store at 25°C (77°F); excursions permitted between 15°-30°C (59°-86°F)

■ tamper evident sealed packets

■ do not use any opened or torn packets

Inactive ingredients

corn starch, hypromellose, maltodextrin, microcrystalline cellulose, polyethylene glycol, sodium lauryl sulfate

Questions or comments? 1-800-634-7680

PACKAGE LABEL

Medi-First®

Pain & Ache

Pain Reliever • Aspirin (NSAID) 500 mg

Pain Reliever Aid • Caffeine 32.5 mg

Fast Acting Advanced Formula

Pull to Open

This Package is for Households Without Young Children.

Tamper Evident Unit Dose Packets

80 Caplets

(40 x 2)

PACKAGE LABEL

Medi-First® Plus

Pain & Ache

Pain Reliever • Aspirin (NSAID) 500 mg

Pain Reliever Aid • Caffeine 32.5 mg

Extra Strength Pain Relief

Fast Acting Advanced Formula

Pull to Open

This Package is for Households Without Young Children.

Tamper Evident Unit Dose Packets

80 Caplets

(40 x 2's)